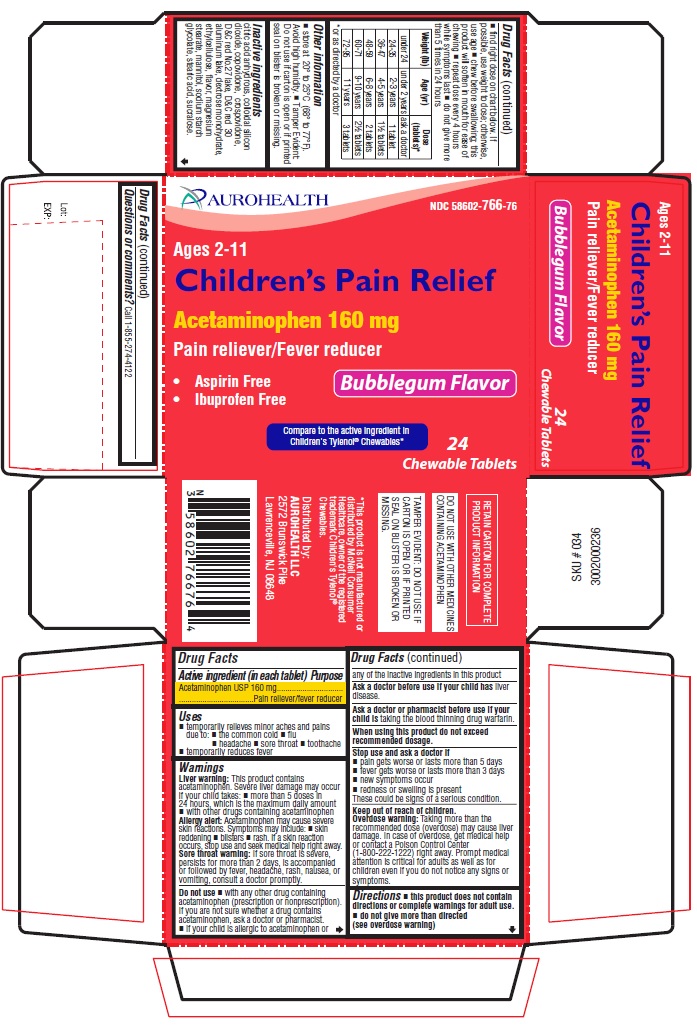 DRUG LABEL: Childrens Pain Relief
NDC: 58602-766 | Form: TABLET, CHEWABLE
Manufacturer: Aurohealth LLC
Category: otc | Type: Human OTC Drug Label
Date: 20250918

ACTIVE INGREDIENTS: ACETAMINOPHEN 160 mg/1 1
INACTIVE INGREDIENTS: ANHYDROUS CITRIC ACID; SILICON DIOXIDE; COPOVIDONE K25-31; CROSPOVIDONE (120 .MU.M); D&C RED NO. 27; D&C RED NO. 30; DEXTROSE MONOHYDRATE; ETHYLCELLULOSE (4 MPA.S); MAGNESIUM STEARATE; MANNITOL; SODIUM STARCH GLYCOLATE TYPE A POTATO; STEARIC ACID; SUCRALOSE

Drug Facts

Active ingredient (in each tablet)

Acetaminophen USP 160 mg

Purpose

Pain reliever/fever reducer

Uses

- temporarily relieves minor aches and pains due to:
  - the common cold
  - flu
  - headache
  - sore throat
  - toothache
- temporarily reduces fever

Warnings

- Liver warning: This product contains acetaminophen. Severe liver damage may occur if your child takes:
  - more than 5 doses in 24 hours, which is the maximum daily amount
  - with other drugs containing acetaminophen
- Allergy alert: Acetaminophen may cause severe skin reactions. Symptoms may include:
  - skin reddening
  - blisters
  - rash.

If a skin reaction occurs, stop use and seek medical help right away.

- Sore throat warning: If sore throat is severe, persists for more than 2 days, is accompanied or followed by fever, headache, rash, nausea, or vomiting, consult a doctor promptly.

Do not use

- with any other drug containing acetaminophen (prescription or nonprescription). If you are not sure whether a drug contains acetaminophen, ask a doctor or pharmacist.
- if your child is allergic to acetaminophen or any of the inactive ingredients in this product.

Ask a doctor before use if your child has

liver disease.

Ask a doctor or pharmacist before use if your child is

taking the blood thinning drug warfarin.

When using this product

do not exceed recommended dosage.

Stop use and ask a doctor if

- pain gets worse or lasts more than 5 days
- fever gets worse or lasts more than 3 days
- new symptoms occur
- redness or swelling is present

These could be signs of a serious condition.

Keep out of reach of children.

Overdose warning: Taking more than the recommended dose (overdose) may cause liver damage. In case of overdose, get medical help or contact a Poison Control Center (1-800-222-1222) right away. Prompt medical attention is critical for adults as well as for children even if you do not notice any signs or symptoms.

Directions

- this product does not contain directions or complete warnings for adult use.
- do not give more than directed (see overdose warning)
- find right dose on chart below. If possible, use weight to dose; otherwise, use age
- chew before swallowing; this product will soften in mouth for ease of chewing
- repeat dose every 4 hours while symptoms last
- do not give more than 5 times in 24 hours

Weight (lb) | Age (yr) | Dose (tablets)*
under 24 | under 2 years | ask a doctor
24-35 | 2-3 years | 1 tablet
36-47 | 4-5 years | 1½ tablets
48-59 | 6-8 years | 2 tablets
60-71 | 9-10 years | 2½ tablets
72-95 | 11 years | 3 tablets
* or as directed by a doctor

Other information

- store at 20° to 25°C (68° to 77°F). Avoid high humidity.
- Tamper Evident: Do not use if carton is open or if printed seal on blister is broken or missing.

Inactive ingredients

citric acid anhydrous, colloidal silicon dioxide, copovidone, crospovidone, D&C red No.27 lake, D&C red 30 aluminum lake, dextrose monohydrate, ethylcellulose, flavor, magnesium stearate, mannitol, sodium starch glycolate, stearic acid, sucralose.

Questions or comments?
Call 1-855-274-4122

* This product is not manufactured or distributed by McNeil Consumer Healthcare, owner of the registered trademark Children's Tylenol® Chewables.
DO NOT USE WITH OTHER MEDICINES CONTAINING ACETAMINOPHEN

Distributed by:
AUROHEALTH LLC
2572 Brunswick Pike
Lawrenceville, NJ 08648

PACKAGE LABEL-PRINCIPAL DISPLAY PANEL - 160 mg (24 Chewable Tablets)

NDC 58602-766-76
Ages 2-11
Children's Pain Relief
Acetaminophen 160 mg
Pain reliever/Fever reducer

- Aspirin Free
- Ibuprofen Free

Bubblegum Flavor
Compare to the active ingredient in
Children's Tylenol® Chewables*
24
Chewable Tablets